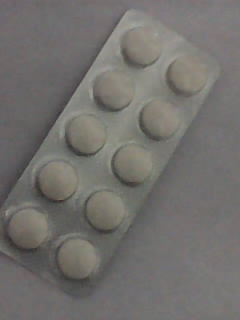 DRUG LABEL: APTIDINE
NDC: 46084-031 | Form: TABLET
Manufacturer: A P J Laboratories Limited
Category: otc | Type: HUMAN OTC DRUG LABEL
Date: 20130221

ACTIVE INGREDIENTS: RANITIDINE HYDROCHLORIDE 75 mg/1 1
INACTIVE INGREDIENTS: CELLULOSE, MICROCRYSTALLINE 80 mg/1 1; STARCH, CORN 30 mg/1 1; POVIDONE K30 10 mg/1 1; METHYLPARABEN 3 mg/1 1; MAGNESIUM STEARATE 20 mg/1 1; TALC 30 mg/1 1; SODIUM STARCH GLYCOLATE TYPE A POTATO 40 mg/1 1; SILICON DIOXIDE 1 mg/1 1

ACTIVE INGREDIENT

RANITIDINE HYDROCHLORIDE

PURPOSE

Acid reducer

KEEP OUT OF REACH OF CHILDREN

In case of overdose, get medical help or contact a Poison Control Center right away.

INDICATIONS AND USAGE

relieves heartburn associated with acid indigestion and sour stomach
prevents heartburn associated with acid indigestion and sour stomach brought on by eating or drinking certain foods and beverages

Allergy alert: Do not use if you are allergic to ranitidine or other acid reducers

DOSAGE AND ADMINISTRATION

adults and children 12 years and over:
to relieve symptoms, swallow 1 tablet with a glass of water
to prevent symptoms, swallow 1 tablet with a glass of water 30 to 60 minutes before eating food or drinking beverages that cause heartburn
can be used up to twice daily (do not take more than 2 tablets in 24 hours)
children under 12 years: ask a doctor

INACTIVE INGREDIENT

CELLULOSE, MICROCRYSTALLINE

INACTIVE INGREDIENT

STARCH, CORN

INACTIVE INGREDIENT

POVIDONE K30

INACTIVE INGREDIENT

METHYLPARABEN

INACTIVE INGREDIENT

MAGNESIUM STEARATE

INACTIVE INGREDIENT

TALC

INACTIVE INGREDIENT

SODIUM STARCH GLYCOLATE TYPE A POTATO

INACTIVE INGREDIENT

SILICON DIOXIDE